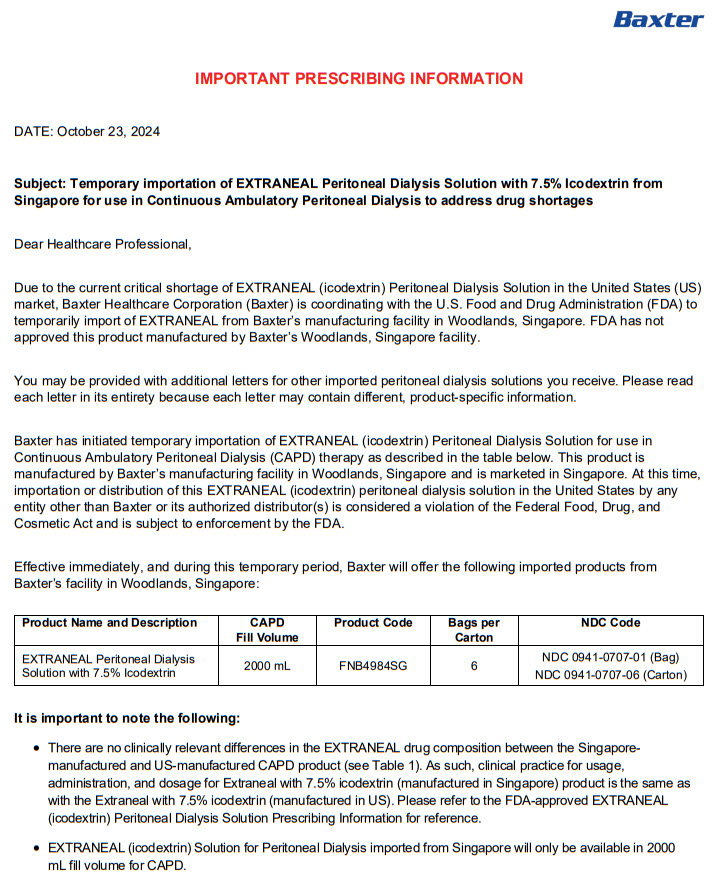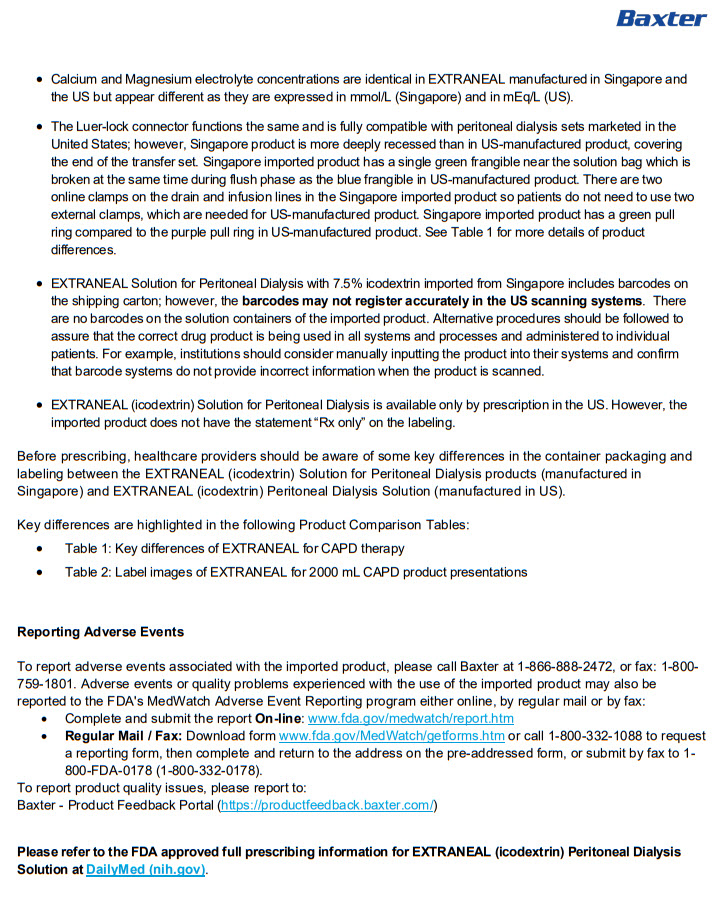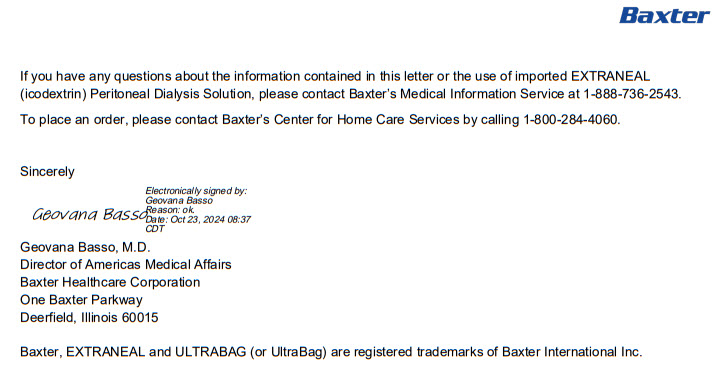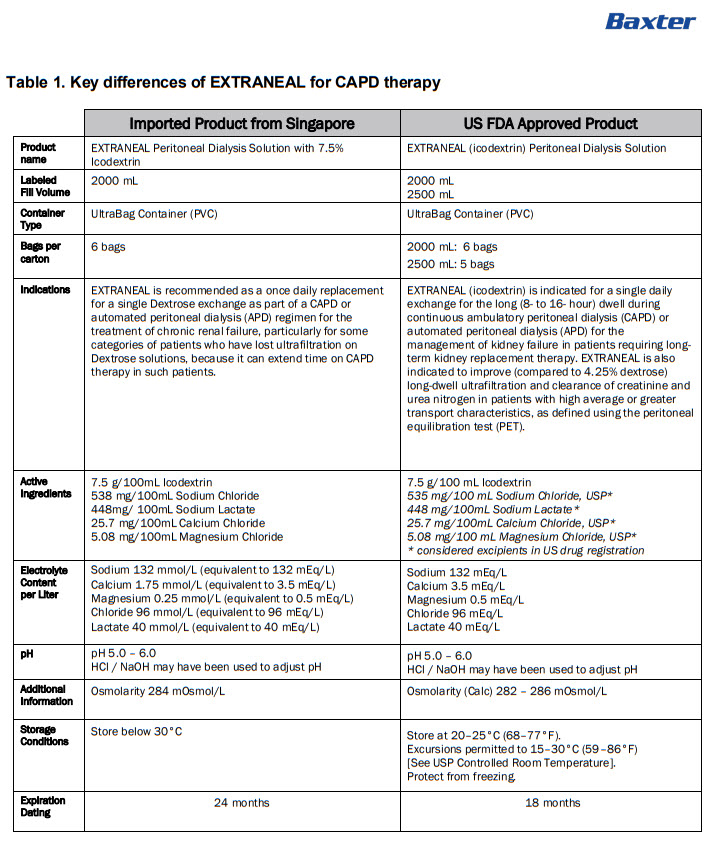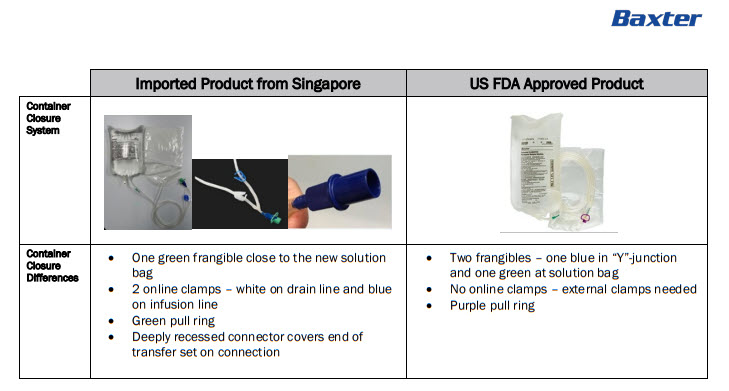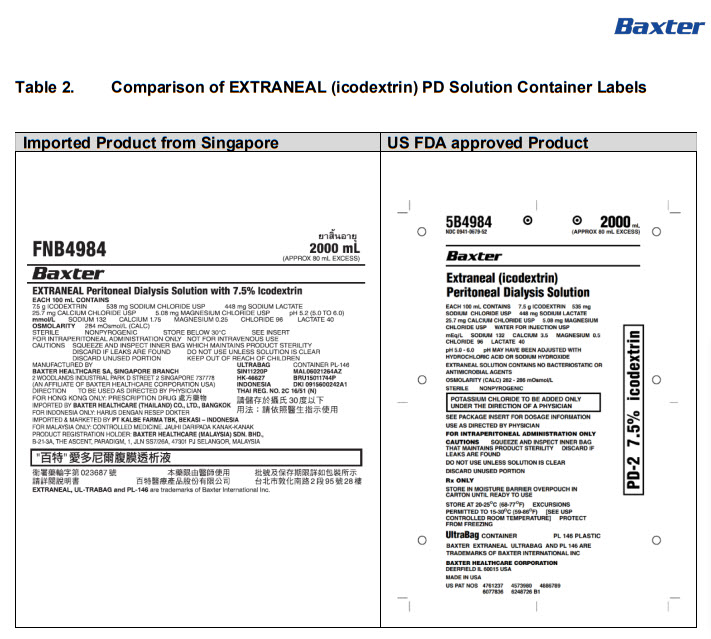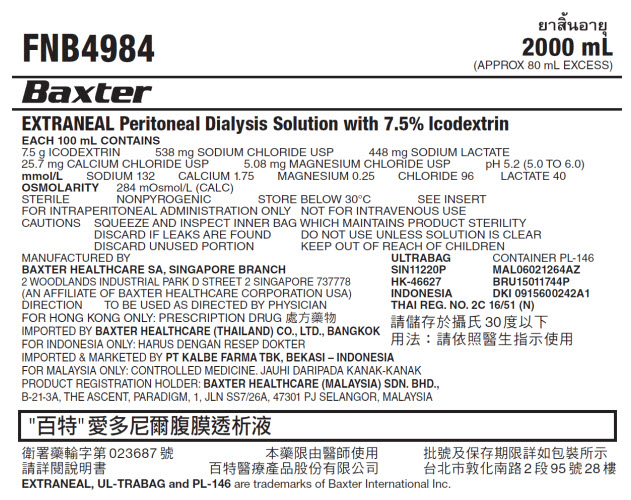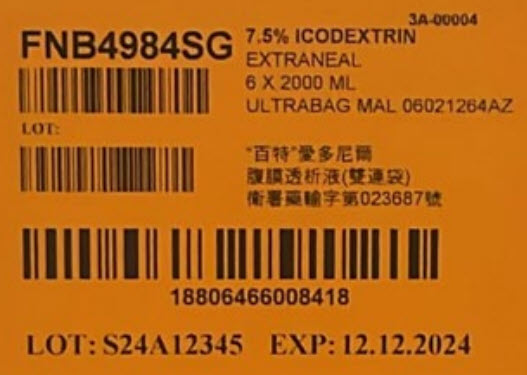 DRUG LABEL: EXTRANEAL
NDC: 0941-0707 | Form: INJECTION, SOLUTION
Manufacturer: Vantive US Healthcare LLC
Category: prescription | Type: HUMAN PRESCRIPTION DRUG LABEL
Date: 20250508

ACTIVE INGREDIENTS: ICODEXTRIN 7.5 g/100 mL; SODIUM CHLORIDE 538 mg/100 mL; SODIUM LACTATE 448 mg/100 mL; CALCIUM CHLORIDE 25.7 mg/100 mL; MAGNESIUM CHLORIDE 5.08 mg/100 mL
INACTIVE INGREDIENTS: WATER; HYDROCHLORIC ACID; SODIUM HYDROXIDE

EXTRANEAL Peritoneal Dialysis Solution with 7.5% icodextrin

PACKAGE/LABEL PRINCIPAL DISPLAY PANEL

FNB4984
2000 mL
(APPROX 80 mL EXCESS)

BaxterLogo

EXTRANEAL Peritoneal Dialysis Solution with 7.5% Icodextrin

EACH 100 mL CONTAINS
7.5 G ICODEXTRIN 538 mg SODIUM CHLORIDE USP 448 mg SODIUM LACTATE
25.7 mg CALCIUM CHLORIDE USP 5.08 mg MAGNESIUM CHLORIDE USP pH 5.2 (5.0 to 6.0)
mmol/LSODIUM 132 CALCIUM 1.75 MAGNESIUM 0.25 CHLORIDE 96 LACTATE 40
OSMOLARITY284 mOsmol/L (CALC)
STERILE NONPYROGENIC STORE BELOW 30°C SEE INSERT
FOR INRAPERITONEAL ADMINISTRATION ONLY NOT FOR INTRAVENOUS USE
CAUTIONS SQUEEZE AND INSPECT INNER BAG WHICH MAINTAINS PRODUCT STERILITY
DISCARD IF LEAKS ARE FOUND DO NOT USE UNLESS SOLUTION IS CLEAR
DISCARD UNUSED PORTION KEEP OUT OF REACH OF CHILDREN

MANUFACTURED BY
BAXTER HEALTHCARE SA, SINGAPORE BRANCH
2 WOODLANDS INDUSTRIAL PARK D STREET 2 SINGAPORE 737778
(AN AFFILIATE OF BAXTER HEALTHCARE CORPORATION USA)
DIRECTION TO BE USED AS DIRECTED BY PHYSICIAN
FOR HONG KONG ONLY: PRESCRIPTION DRUG
IMPORTED BY BAXTER HEALTHCARE (THAILAND) CO., LTD., BANGKOK
FOR INDONESIA ONLY: HARUS DENGAN RESEP DOKTER
IMPORTED & MARKETED BY PT KALBE FARMA TBK, BEKSAI – INDONESIA
FOR MALAYSIA ONLY: CONTROLLED MEDICINE. JAUHI DARIPADA KANAK-KANAK
PRODUCT REGISTRATION HOLDER: BAXTER HEALTHCARE (MALAYSIA) SDN. BHD.,
B-21-3A, THE ASCENT, PARADIGM, 1, JLN SS7/26A, 47301 PJ SELANGOR, MALAYSIA

ULTRABAGCONTAINER PL-146
SIN11220P MAL06021264AZ
HK-46627 BRU15011744P
INDONESIA DKI 0915600242A1
THAI REG. NO. 2C 16/51 (N)

30

023687

2 95 28

EXTRANEAL, UL-TRABAG and PL-146are trademarks of Baxter International Inc.

3A-00004

FNB4984SG
barcode
Lot:
barcode

7.5% ICODEXTRIN
EXTRANEAL
6 X 2000 ML
ULTRABAG MAL 06021264AZ

023687

Barcode
18806466008418

LOT: S24A12345
EXP: 12.12.2024